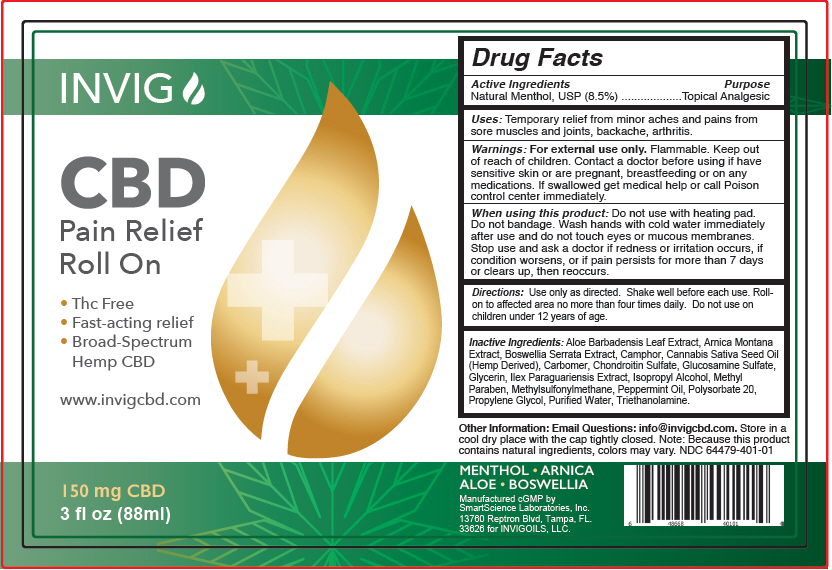 DRUG LABEL: CBD Pain Relief Roll On
NDC: 64479-401 | Form: GEL
Manufacturer: SmartScience Laboratories, Inc.
Category: otc | Type: HUMAN OTC DRUG LABEL
Date: 20200210

ACTIVE INGREDIENTS: Menthol, Unspecified Form 85 mg/1 mL
INACTIVE INGREDIENTS: ALOE VERA LEAF; ARNICA MONTANA; INDIAN FRANKINCENSE; CAMPHOR (SYNTHETIC); CANNABIS SATIVA SEED OIL; CARBOMER INTERPOLYMER TYPE A (ALLYL SUCROSE CROSSLINKED); CHONDROITIN SULFATE (SHARK); GLUCOSAMINE SULFATE POTASSIUM CHLORIDE; GLYCERIN; ILEX PARAGUARIENSIS LEAF; ISOPROPYL ALCOHOL; METHYLPARABEN; DIMETHYL SULFONE; PEPPERMINT OIL; POLYSORBATE 20; PROPYLENE GLYCOL; TROLAMINE; WATER

CBD Pain Relief Roll On

Drug Facts

Active Ingredients

Natural Menthol, USP (8.5%)

Purpose

Topical Analgesic

Uses

Temporary relief from minor aches and pains from sore muscles and joints, backache, arthritis.

Warnings

For external use only. Flammable.

Keep out of reach of children.

ASK DOCTOR

Contact a doctor before using if have sensitive skin or are pregnant, breastfeeding or on any medications. If swallowed get medical help or call Poison control center immediately.

When using this product

Do not use with heating pad. Do not bandage. Wash hands with cold water immediately after use and do not touch eyes or mucous membranes. Stop use and ask a doctor if redness or irritation occurs, if condition worsens, or if pain persists for more than 7 days or clears up, then reoccurs.

Directions

Use only as directed. Shake well before each use. Roll-on to affected area no more than four times daily. Do not use on children under 12 years of age.

Inactive Ingredients

Aloe Barbadensis Leaf Extract, Arnica Montana Extract, Boswellia Serrata Extract, Camphor, Cannabis Sativa Seed Oil (Hemp Derived), Carbomer, Chondroitin Sulfate, Glucosamine Sulfate, Glycerin, Ilex Paraguariensis Extract, Isopropyl Alcohol, Methyl Paraben, Methylsulfonylmethane, Peppermint Oil, Polysorbate 20, Propylene Glycol, Purified Water, Triethanolamine.

Other Information

Email Questions: info@invigcbd.com. Store in a cool dry place with the cap tightly closed. Note: Because this product contains natural ingredients, colors may vary. NDC 64479-401-01

Manufactured cGMP by
Smart Science Labs,
13760 Reptron Blvd Tampa, FL. 33626

PRINCIPAL DISPLAY PANEL - 88 ml Bottle Label

INVIG

CBD
Pain Relief
Roll On

- Thc Free
- Fast-acting relief
- Broad-Spectrum
  Hemp CBD

www.invigcbd.com

150 mg CBD
3 fl oz (88ml)